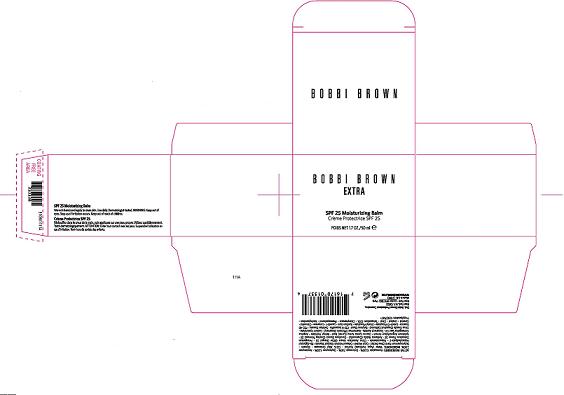 DRUG LABEL: BOBBI BROWN EXTRA
NDC: 64141-916 | Form: CREAM
Manufacturer: BOBBI BROWN PROFESSIONAL COSMETICS INC
Category: otc | Type: HUMAN OTC DRUG LABEL
Date: 20100414

ACTIVE INGREDIENTS: HOMOSALATE 10 mL/100 mL; OCTINOXATE 7.5 mL/100 mL; OXYBENZONE 5.0 mL/100 mL; AVOBENZONE 2.0 mL/100 mL

ACTIVE INGREDIENT

ACTIVE INGREDIENTS: HOMOSALATE 10.00% [] OCTINOXATE 7.50% [] OXYBENZONE 5.00% [] AVOBENZONE 2.00%

WARNINGS

WARNING: KEEP OUT OF EYES. STOP USE IF IRRITATION OCCURS.

WHEN USING

DIRECTIONS: WARM IN HANDS AND APPLY TO CLEAN SKIN

PACKAGE LABEL

PRINCIPAL DISPLAY PANEL:

BOBBI BROWN

EXTRA

SPF 25 MOISTURIZING BALM

POIDS NET. 1.7 OZ / 50 ML
BOBBI BROWN PROFESSIONAL COSMETICS
NEW YORK, NY 10022
E109
WWW.BOBBIBROWN.COM